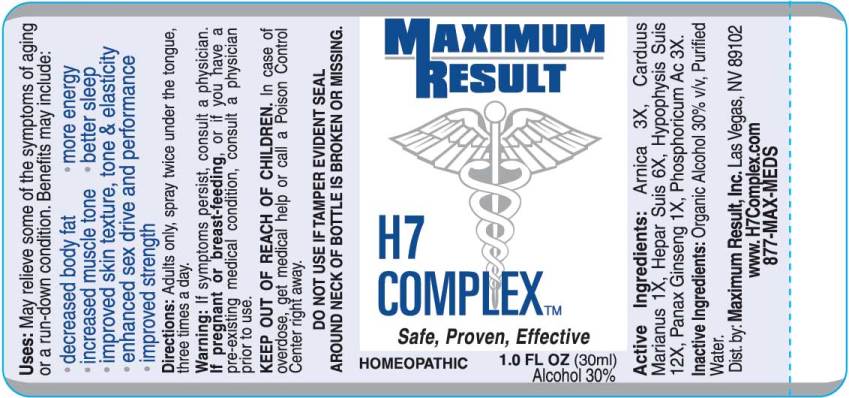 DRUG LABEL: H7 Complex
NDC: 49415-0005 | Form: SPRAY
Manufacturer: Maximum Results Solution, Inc.
Category: homeopathic | Type: HUMAN OTC DRUG LABEL
Date: 20171129

ACTIVE INGREDIENTS: ARNICA MONTANA 3 [hp_X]/1 mL; SILYBUM MARIANUM SEED 1 [hp_X]/1 mL; PORK LIVER 6 [hp_X]/1 mL; SUS SCROFA PITUITARY GLAND 12 [hp_X]/1 mL; ASIAN GINSENG 1 [hp_X]/1 mL; PHOSPHORIC ACID 3 [hp_X]/1 mL
INACTIVE INGREDIENTS: WATER; ALCOHOL

Drug Facts:

ACTIVE INGREDIENTS:

Arnica Montana 3X, Carduus Marianus 1X, Hepar Suis 6X, Hypophysis Suis 12X, Panax Ginseng 1X, Phosphoricum Acidum 3X.

USES:

May relieve some of the symptoms of aging or a run-down condition. Benefits may include:
• decreased body fat
• increased muscle tone
• improved skin texture, tone & elasticity
• enhanced sex drive and performance
• improved strength
• more energy
• better sleep

WARNINGS:

If symptoms persist, consult a physician.
If pregnant or breast-feeding, or if you have a pre-existing medical condition, consult a physician prior to use.
KEEP OUT OF REACH OF CHILDREN. In case of overdose, get medical help or call a Poison Control Center right away.
DO NOT USE IF TAMPER EVIDENT SEAL AROUND NECK OF BOTTLE IS BROKEN OR MISSING.

KEEP OUT OF REACH OF CHILDREN. In case of overdose, get medical help or call a Poison Control Center right away.

DIRECTIONS:

Adults only, spray twice under the tongue, three times a day.

INDICATIONS:

May relieve some of the symptoms of aging or a run-down condition. Benefits may include:
• decreased body fat
• increased muscle tone
• improved skin texture, tone & elasticity
• enhanced sex drive and performance
• improved strength
• more energy
• better sleep

INACTIVE INGREDIENTS:

Organic Alcohol 30% v/v, Purified Water

QUESTIONS:

Dist. by: Maximum Result, Inc. Las Vegas, NV 89102
www.Doctors-Choice-HGH.com
877-MAX-MEDS

PACKAGE LABEL DISPLAY:

MAXIMUM

RESULT

H7

COMPLEX

Safe, Proven, Effective

HOMEOPATHIC 1.0 FL OZ (30ml)